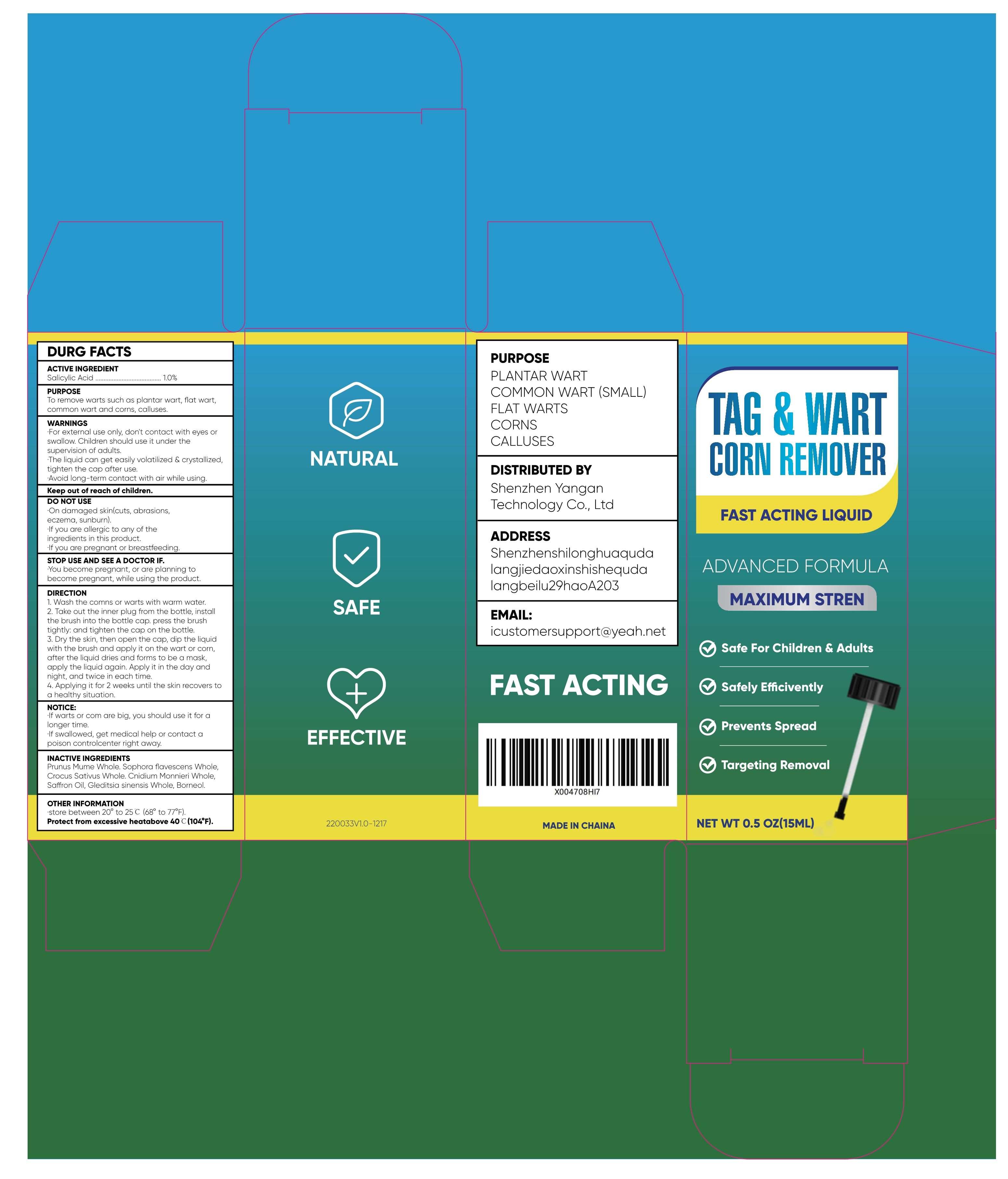 DRUG LABEL: FAST ACTING WART REMOVER
NDC: 84023-115 | Form: LIQUID
Manufacturer: Shenzhen Yangan Technology Co., Ltd.
Category: otc | Type: HUMAN OTC DRUG LABEL
Date: 20250324

ACTIVE INGREDIENTS: SALICYLIC ACID 1 mg/100 mL
INACTIVE INGREDIENTS: BORNEOL; PRUNUS MUME WHOLE; CROCUS SATIVUS WHOLE; SOPHORA FLAVESCENS WHOLE; CNIDIUM MONNIERI WHOLE; GLEDITSIA SINENSIS WHOLE; SAFFRON OIL

FAST ACTING WART REMOVER LIQUID

ACTIVE INGREDIENT

Salicylic Acid................1.0%

PURPOSE

To remove warts such as plantar wart, flat wart, common wart and corns, calluses.

DO NOT USE

·On damaged skin(cuts, abrasions, eczema, sunburn).

·If you are allergic to any of the ingredients in this product.

·If you are pregnant or breastfeeding.

Keep out of reach of children.

STOP USE

·You become pregnant, or are planning to become pregnant, while using the product.

WARNINGS

·For external use only, don't contact with eyes or swallow. Children should use it under the supervision of adults.

·The liquid can get easily volatilized & crystallized, tighten the cap after use.

·Avoid long-term contact with air while using.

OTHER SAFETY INFORMATION

NOTICE：

·If warts or com are big, you should use it for alonger time.

·If swallowed, get medical help or contact apoison controlcenter right away.

INACTIVE INGREDIENT

Prunus Mume Whole. Sophora flavescens Whole, Crocus Sativus Whole. Cnidium Monnieri Whole, Saffron Oil, Gleditsia sinensis Whole, Borneol.

DOSAGE AND ADMINISTRATION

DIRECTION

1. Wash the comns or warts with warm water.

2. Take out the inner plug from the bottle, install the brush into the bottle cap. press the brush tightly: and tighten the cap on the bottle.

3. Dry the skin, then open the cap, dip the liquid with the brush and apply it on the wart or corn, after the liquid dries and forms to be a mask, apply the liquid again. Apply it in the day and night, and twice in each time.

4. Applying it for 2 weeks until the skin recovers to a healthy situation.

INDICATIONS AND USAGE

1. Wash the corns or warts with warm water.

2. Take out the inner plug from the bottle, install the brush into the bottle cap. press the brush tightly: and tighten the cap on the bottle.

3. Dry the skin, then open the cap, dip the liquid with the brush and apply it on the wart or corn, after the liquid dries and forms to be a mask, apply the liquid again. Apply it in the day and night, and twice in each time.

4. Applying it for 2 weeks until the skin recovers to a healthy situation.